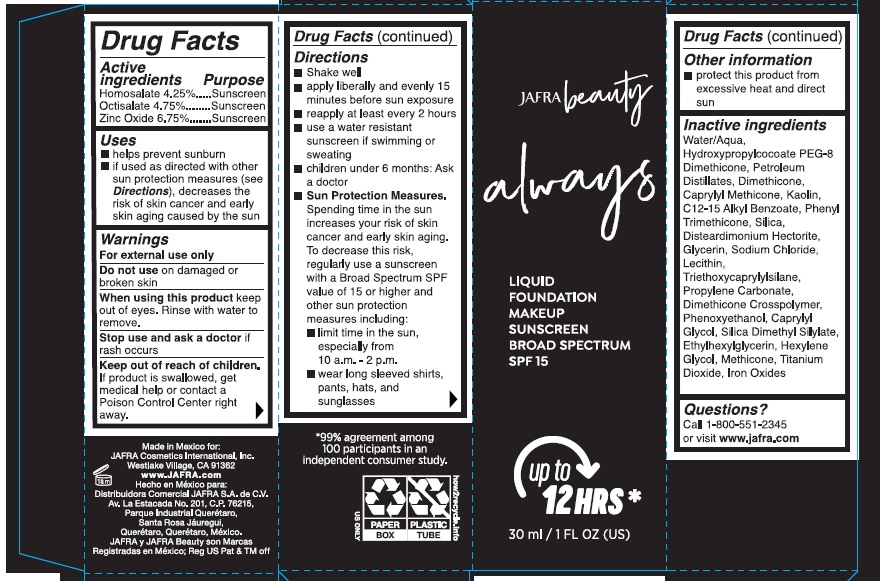 DRUG LABEL: Always Liquid Foundation Makeup Sunscreen Broad Spectrum SPF 15 - Ivory
NDC: 68828-806 | Form: LIQUID
Manufacturer: Distribuidora Comercial Jafra, S.A. de C.V
Category: otc | Type: HUMAN OTC DRUG LABEL
Date: 20251021

ACTIVE INGREDIENTS: OCTISALATE 4.75 g/100 mL; ZINC OXIDE 6.75 g/100 mL; HOMOSALATE 4.25 g/100 mL
INACTIVE INGREDIENTS: SILICON DIOXIDE; HYDROXYPROPYLCOCOATE PEG-8 DIMETHICONE; TITANIUM DIOXIDE; DIMETHICONE CROSSPOLYMER; ETHYLHEXYLGLYCERIN; GLYCERIN; METHICONE (20 CST); PHENYL TRIMETHICONE; SILICA DIMETHYL SILYLATE; PROPYLENE CARBONATE; SODIUM CHLORIDE; TRIETHOXYCAPRYLYLSILANE; WATER; FERROSOFERRIC OXIDE; DIMETHICONE; HEXYLENE GLYCOL; CAPRYLYL TRISILOXANE; PHENOXYETHANOL; KAOLIN; CAPRYLYL GLYCOL; FERRIC OXIDE RED; FERRIC OXIDE YELLOW; LECITHIN, SOYBEAN; ALKYL (C12-15) BENZOATE; DISTEARDIMONIUM HECTORITE; C13-14 ISOPARAFFIN

Always Liquid Foundation Makeup Sunscreen Broad Spectrum SPF 15 -Ivory

Active ingredients

Homosalate 4.25%

Octisalate 4.75%

Zinc Oxide 6.75%

Purpose

Sunscreen

Uses

helps prevent sunburn

if used as directed with other sun protection measures (see Directions), decreases the risk of skin cancer and early skin aging caused by the sun

Warnings

For external use only

Do not use on damaged or broken skin

When using this product keep out of eyes. Rinse with water to remove.

Stop use and ask a doctor if rash occurs

Keep out of reach of children. If product is swallowed, get medical help or contact a Poison Control Center right away.

Directions

- Shake well
- apply liberally and evenly 15 minutes before sun exposure
- reapply at least every 2 hours
- use a water resistant sunscreen if swimming or sweating
- children under 6 months: Ask a doctor
- Sun Protection Measures.Spending time in the sun increases your risk of skin cancer and early skin aging. To decrease this risk, regularly use a sunscreen with a Broad Spectrum SPF of 15 or higher and other sun protection measures including:
- limit time in the sun, especially from 10 a.m. – 2 p.m.
- wear long-sleeved shirts, pants, hats, and sunglasses

Other information

protect this product from excessive heat and direct sun

Inactive Ingredients.

Water, Hydroxypropylcocoate PEG-8 Dimethicone, Petroleum Distillates, Dimethicone, Caprylyl Methicone, Kaolin, C12-15 Alkyl Benzoate, Phenyl Trimethicone, Silica, Disteardimonium Hectorite, Glycerin , Sodium Chloride, Lecithin, Triethoxycaprylylsilane, Propylene Carbonate, Dimethicone Crosspolymer, Phenoxyethanol, Caprylyl Glycol, Silica Dimethyl Silylate, Ethylhexylglycerin, Hexylene Glycol, Methicone, Titanium Dioxide, Iron Oxides

Questions?

Call 1-800-551-2345 or visit www.jafra.com